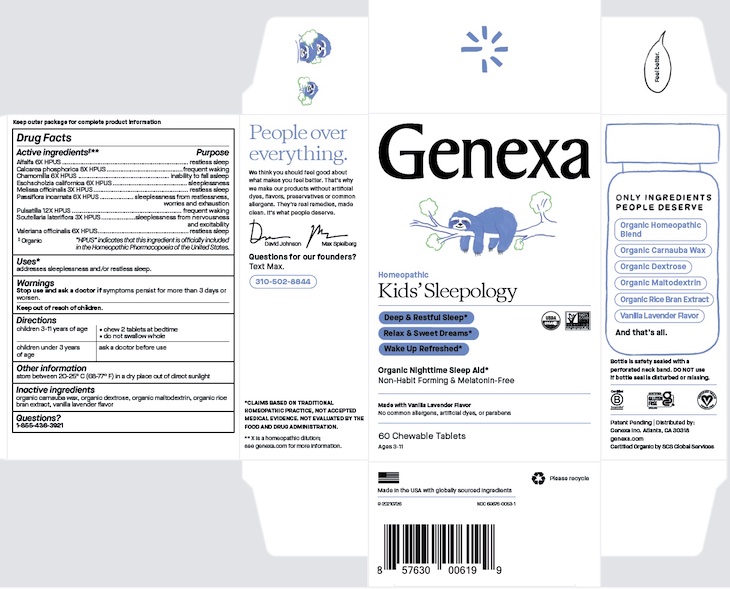 DRUG LABEL: Genexa Kids Sleepology
NDC: 69676-0053 | Form: TABLET, CHEWABLE
Manufacturer: Genexa Inc.
Category: homeopathic | Type: HUMAN OTC DRUG LABEL
Date: 20250226

ACTIVE INGREDIENTS: ESCHSCHOLZIA CALIFORNICA 6 [hp_X]/1 1; PASSIFLORA INCARNATA FLOWERING TOP 6 [hp_X]/1 1; VALERIAN 6 [hp_X]/1 1; MATRICARIA CHAMOMILLA WHOLE 6 [hp_X]/1 1; TRIBASIC CALCIUM PHOSPHATE 8 [hp_X]/1 1; SCUTELLARIA LATERIFLORA TOP 3 [hp_X]/1 1; MELISSA OFFICINALIS LEAF 3 [hp_X]/1 1; PULSATILLA VULGARIS 12 [hp_X]/1 1; ALFALFA 6 [hp_X]/1 1
INACTIVE INGREDIENTS: CARNAUBA WAX; MALTODEXTRIN; RICE BRAN; DEXTROSE

KIDS' SLEEPOLOGY

Keep outer package for complete product information

Drug Facts

Active ingredients‡**

Alfalfa 6X HPUS

Calcarea phosphorica 8X HPUS

Chamomilla 6X HPUS

Eschscholtzia californica 6X HPUS

Melissa officinalis 3X HPUS

Passiflora incarnata 6X HPUS

Pulsatilla 12X HPUS

Scutellaria lateriflora 3X HPUS

Valeriana officinalis 6X HPUS

‡ Organic

"HPUS" indicates that this ingredient is officially included in the Homoeopathic Pharmacopoeia of the United States.

Purpose

restless sleep

frequent waking

inability to fall asleep

sleeplessness

restless sleep

sleeplessness from restlessness, worries and exhaustion

frequent waking

sleeplessness from nervousness and excitability

restless sleep

Uses*

addresses sleeplessness and/or restless sleep.

Warnings

Stop use and ask a doctorif symptoms persist for more than 3 days or worsen.

Keep out of reach of children.

Directions

children 3-11 years of age | - chew 2 tablets at bedtime - do not swallow whole
children under 3 years of age | ask a doctor before use

Other information

store between 20°-25°C (68°-77°F) in a dry place out of direct sunlight

Inactive ingredients

organic carnuaba wax, organic dextrose, organic maltodextrin, organic rice bran extract, vanilla lavender flavor

Questions?

1-855-436-3921

* CLAIMS BASED ON TRADITIONAL HOMEOPATHIC PRACTICE, NOT ACCEPTED MEDICAL EVIDENCE. NOT EVALUATED BY THE FOOD AND DRUG ADMINISTRATION.
** X is a homeopathic dilution: see genexa.com for more information.

Bottle is safety sealed with a perforated neckband. DO NOT use if bottle seal is disturbed or missing.

Patent Pending | Distributed by:

Genexa Inc. Atlanta, GA 30318

genexa.com
Certified Organic by SCS Global Services

Made in the USA with globally sourced ingredients

NDC 69676-0053-1

PACKAGE LABEL

Genexa

Homeopathic

Kids' Sleepology

Deep and Restful Sleep*

Relax and Sweet Dreams*

Wake Up Refreshed*

Organic Nighttime Sleep Aid*

Non-Habit Forming and Melatonin-Free

Made with Vanilla Lavender Flavor

No common allergens, artificial dyes or parabens

60 Chewable Tablets

Ages 3-11